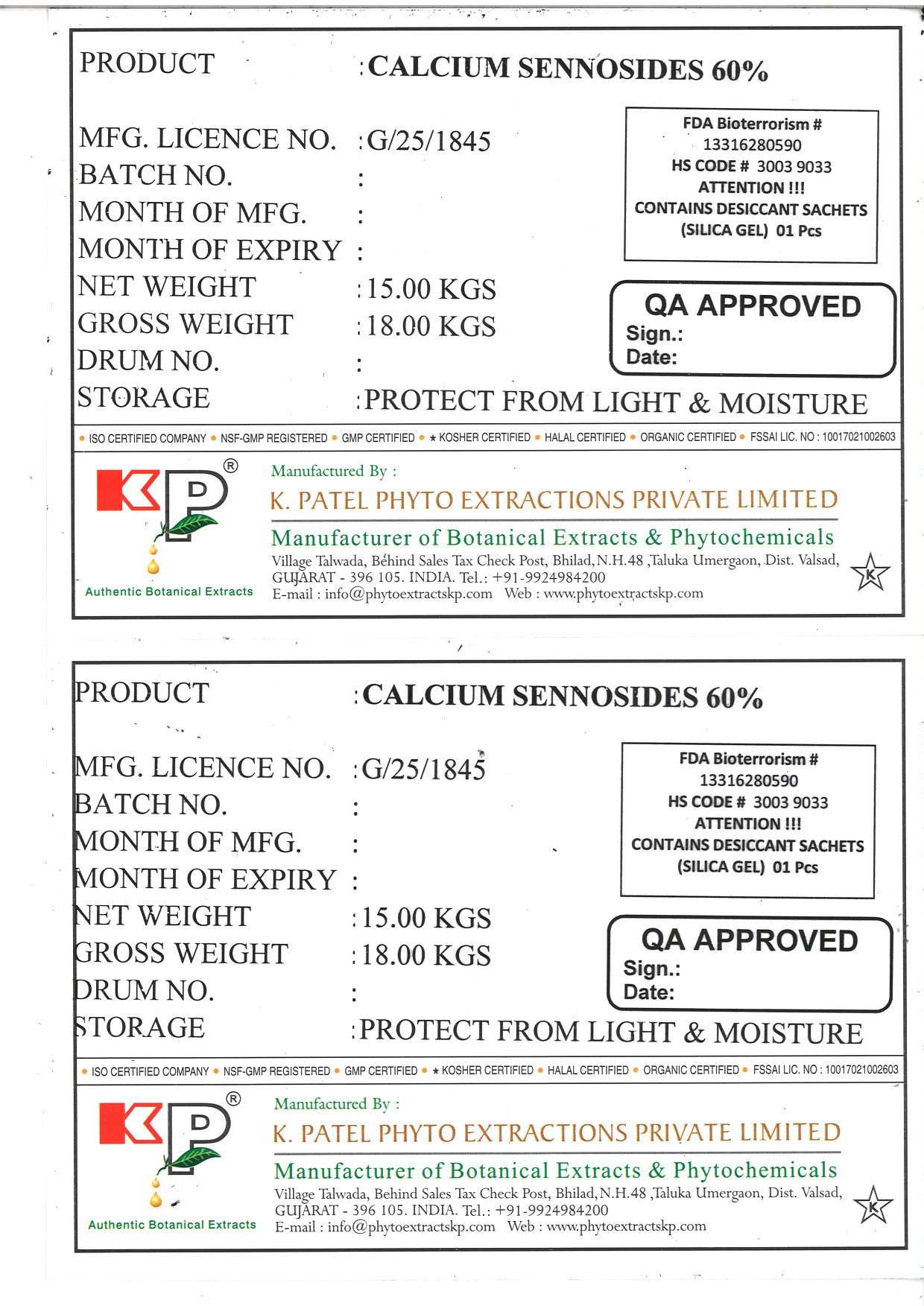 DRUG LABEL: Calcium Sennosides
NDC: 73276-002 | Form: POWDER
Manufacturer: K PATEL PHYTO EXTRACTIONS PRIVATE LIMITED
Category: other | Type: BULK INGREDIENT
Date: 20230110

ACTIVE INGREDIENTS: SENNOSIDES 15 kg/15 kg

Calcium Sennosides 60%